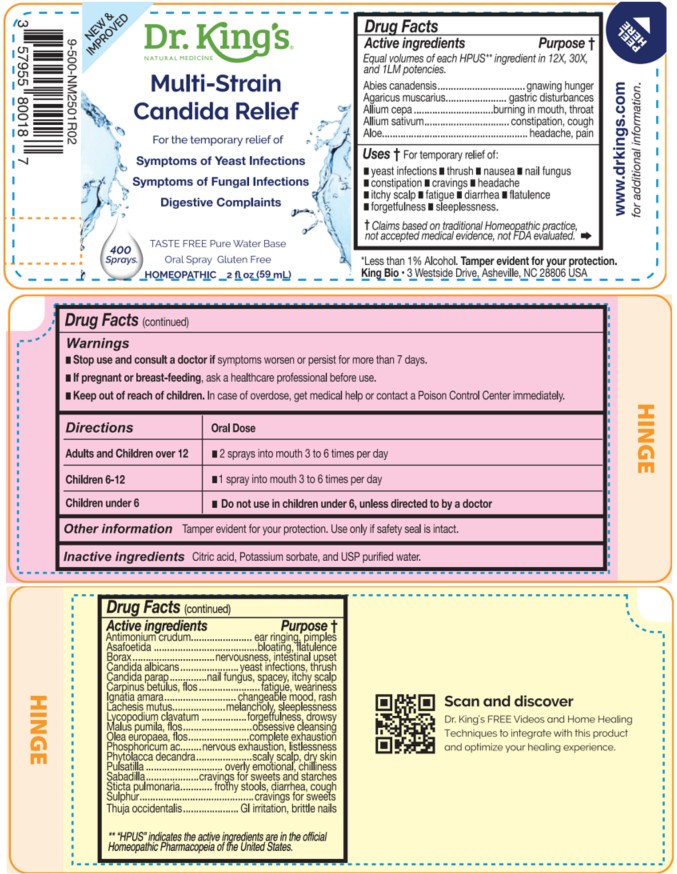 DRUG LABEL: Multi-Strain Candida Relief
NDC: 57955-9998 | Form: LIQUID
Manufacturer: King Bio Inc.
Category: homeopathic | Type: HUMAN OTC DRUG LABEL
Date: 20260302

ACTIVE INGREDIENTS: TSUGA CANADENSIS BARK 12 [hp_X]/59 mL; TSUGA CANADENSIS FLOWER BUD 12 [hp_X]/59 mL; AMANITA MUSCARIA FRUITING BODY 12 [hp_X]/59 mL; ONION 12 [hp_X]/59 mL; GARLIC 12 [hp_X]/59 mL; ALOE 12 [hp_X]/59 mL; ANTIMONY TRISULFIDE 12 [hp_X]/59 mL; FERULA ASSA-FOETIDA RESIN 12 [hp_X]/59 mL; SODIUM BORATE 12 [hp_X]/59 mL; CANDIDA ALBICANS 12 [hp_X]/59 mL; CANDIDA PARAPSILOSIS 12 [hp_X]/59 mL; CARPINUS BETULUS FLOWERING TOP 12 [hp_X]/59 mL; STRYCHNOS IGNATII SEED 12 [hp_X]/59 mL; LACHESIS MUTA VENOM 12 [hp_X]/59 mL; LYCOPODIUM CLAVATUM SPORE 12 [hp_X]/59 mL; MALUS DOMESTICA FLOWER 12 [hp_X]/59 mL; OLEA EUROPAEA FLOWER 12 [hp_X]/59 mL; PHOSPHORIC ACID 12 [hp_X]/59 mL; PHYTOLACCA AMERICANA ROOT 12 [hp_X]/59 mL; PULSATILLA VULGARIS WHOLE 12 [hp_X]/59 mL; SCHOENOCAULON OFFICINALE SEED 12 [hp_X]/59 mL; LOBARIA PULMONARIA 12 [hp_X]/59 mL; SULFUR 12 [hp_X]/59 mL; THUJA OCCIDENTALIS LEAFY TWIG 12 [hp_X]/59 mL
INACTIVE INGREDIENTS: ANHYDROUS CITRIC ACID; POTASSIUM SORBATE; WATER

Multi-Strain Candida Relief

DOSAGE AND ADMINISTRATION

Directions | Oral Dose
Adults and Children over 12 | - 2 sprays into mouth 3 to 6 times per day
Children 6-12 | - 1 spray into mouth 3 to 6 times per day
Children under 6 | - Do not use in children under 6, unless directed to by a doctor

Other information

Tamper evident for your protection. Use only if safety seal is intact.

Scan and discover Dr. King's FREE Videos and Home Healing
Techniques to integrate with this product and optimize your healing experience.

King Bio, Inc. 3 Westside Drive

Asheville, NC 28806 USA

For latest product information and instructions: www.DrKings.com

Inactive Ingredients

Citric acid, Potassium sorbate, and USP purified water,

Active ingredients

Equal volumes of each HPUS** ingredient in 12X,
30X, and 1LM potencies.

Abies canadensis, Agaricus muscarius, Allium cepa, Allium sativum, Aloe, Antimonium crudum, Asafoetida, Borax, Candida albicans, Candida parapsilosis, Carpinus betulus, flos, Ignatia Amara, Lachesis mutus, Lycopodium clavatum, Malus Pumila, flos, Olea europaea, flos, Phosphoricum acidum, Phytolacca decandra, Pulsatilla, Sabadilla, Sticta pulmonaria, Sulphur and Thuja occidentalis.

** "The designation 'HPUS’ means that the active ingredient(s) in this product complies with a monograph (or Monographs) in the Homeopathic Pharmacopeia of the United States.″

INDICATIONS AND USAGE

Uses † For temporary relief of:

█ yeast infections

█ thrush

█ nausea

█ nail fungus

█ constipation

█ cravings

█ headache

█ itchy scalp

█ fatigue

█ diarrhea

█ flatulence

█ forgetfulness

█ sleeplessness

Warnings

Stop use and consult a doctor if symptoms worsen or
persist for more than 7 days.

If pregnant or breast-feeding, ask a healthcare professional
before use.

Keep out of reach of children.

In case of overdose, get medical help or contact a Poison Control Center immediately.

PURPOSE

Equal volumes of each HPUS** ingredient in 12X, 30X, and 1LM potencies.

Active ingredients Purpose †

Abies canadensis.........................................................................gnawing hunger
Agaricus muscarius ...............................................................gastric disturbances
Allium cepa.....................................................................burning in mouth, throat
Allium sativum.......................................................................constipation, cough

Aloe ...........................................................................................headache, pain
Antimonium crudum ...............................................................ear ringing, pimples
Asafoetida...............................................................................bloating, flatulence
Borax ...................................................................... nervousness, intestinal upset
Candida albicans ................................................................yeast infections, thrush
Candida parapsilosis.................................................nail fungus, spacey, itchy scalp
Carpinus betulus, flos................................................................ fatigue, weariness
Ignatia amara....................................................................changeable mood, rash
Lachesis mutus...............................................................melancholy, sleeplessness
Lycopodium clavatum.............................................................forgetfulness, drowsy
Malus pumila, flos ...................................................................obsessive cleansing
Olea europaea, flos............................................................... complete exhaustion
Phosphoricum acidum.............................................nervous exhaustion, listlessness
Phytolacca decandra................................................................scaly scalp, dry skin
Pulsatilla .....................................................................overly emotional, chilliness
Sabadilla..............................................................cravings for sweets and starches
Sticta pulmonaria ..................................................... frothy stools, diarrhea, cough
Sulphur ..................................................................................cravings for sweets
Thuja occidentalis .............................................................GI irritation, brittle nails

** "The designation 'HPUS’ means that the active ingredient(s) in this product complies with a monograph (or Monographs) in the Homeopathic Pharmacopeia of the United States.″

† Claims based on traditional Homeopathic practice, not accepted medical evidence, not
FDA evaluated.